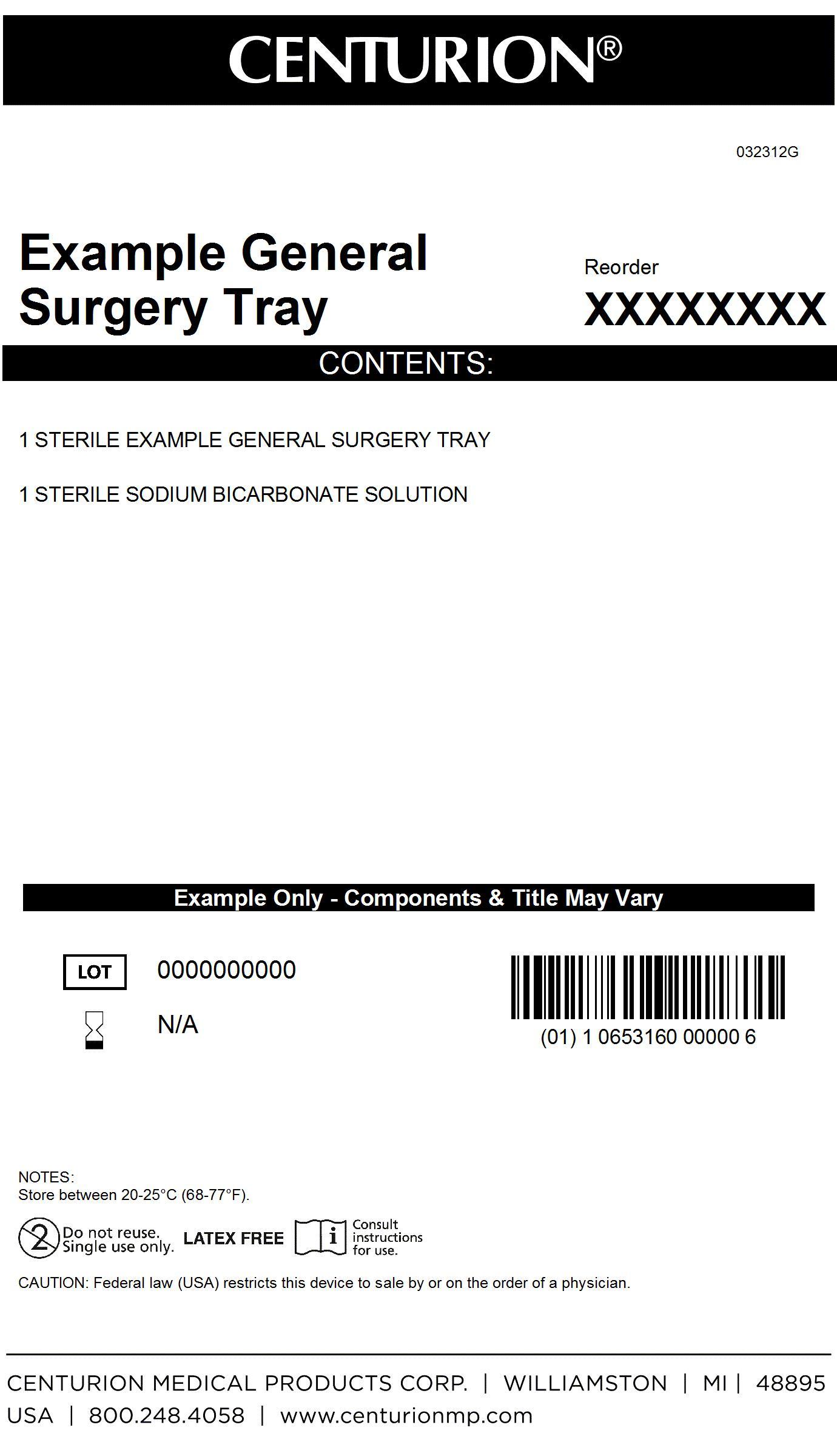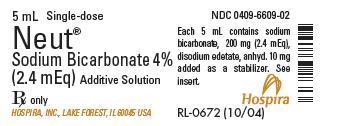 DRUG LABEL: General Surgery Kit
NDC: 24840-1580 | Form: KIT | Route: INTRAVENOUS
Manufacturer: Centurion Medical Products
Category: other | Type: MEDICAL DEVICE
Date: 20131112

ACTIVE INGREDIENTS: SODIUM BICARBONATE 0.2 g/5 mL
INACTIVE INGREDIENTS: water; EDETATE DISODIUM ANHYDROUS

General Surgery Tray

DESCRIPTION

Neut (4% sodium bicarbonate additive solution) is a sterile, nonpyrogenic solution of sodium bicarbonate in water for injection. It is administered by the intravenous route only after addition as a neutralizing agent to an acidic large volume parenteral solution. Each 5 mL contains sodium bicarbonate 0.2 g (2.4 mEq each of Na^+ and HCO3^-); edetate disodium, anhydrous 10 mg added as a stabilizer. Total sodium (Na+) content of each 5 mL is 56.1 mg (11.2 mg/mL).

The solutions contain no bacteriostat, antimicrobial agent or added buffer; pH 8.0 (7.0 to 8.5).

Sodium Bicarbonate, USP is chemically designated as NaHCO3, a white crystalline powder soluble in water.